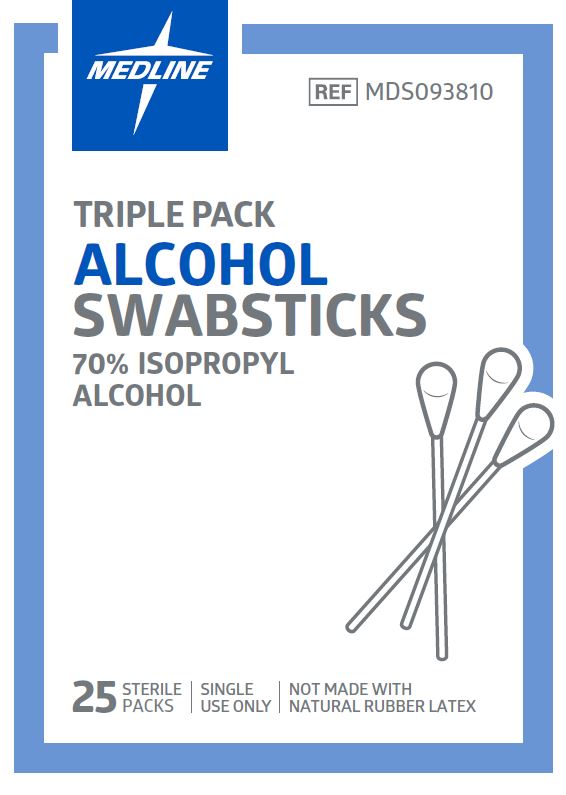 DRUG LABEL: Medline Alcohol Swabstick
NDC: 53329-807 | Form: SWAB
Manufacturer: Medline Industries, LP
Category: otc | Type: HUMAN OTC DRUG LABEL
Date: 20241213

ACTIVE INGREDIENTS: ISOPROPYL ALCOHOL 70 mL/100 mL
INACTIVE INGREDIENTS: WATER

807 Medline Alcohol Swabsticks

Active ingredient

Isopropyl alcohol 70% v/v

Purpose

Antiseptic

Uses

- for preparation of the skin prior to injection

Warnings

For external use only.

Flammable, keep away from fire or flame.

Do not use

- with electrocautery procedures
- in the eyes

Stop use and ask a doctor if

- irritation and redness develop
- condition persists for more than 72 hours

Keep out of reach of children.

If swallowed, get medical help or contact a Poison Control Center right away.

Directions

- apply as needed
- discard after a single use

Other information

- protect from freezing, avoid excessive heat
- do not flush
- not made with natural rubber latex

Inactive ingredient

water

Manufacturing Information

Manufactured for:

Medlien Industries, LP

Three Lakes Drive, Northfield, IL 60093 USA

Made in China

www.medline.com

1-800-MEDLINE (633-5463)

REF: MDS093810

V2 RF22LPD